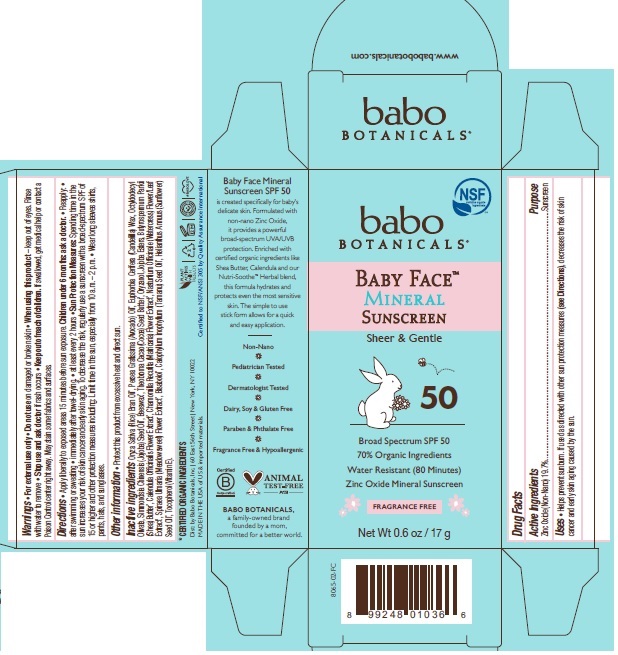 DRUG LABEL: Babo Baby Face Mineral Sunscreen
NDC: 79265-8065 | Form: STICK
Manufacturer: Babo Botanicals, Inc.
Category: otc | Type: HUMAN OTC DRUG LABEL
Date: 20241212

ACTIVE INGREDIENTS: ZINC OXIDE 20.267 g/100 g
INACTIVE INGREDIENTS: TAMANU OIL 0.01 mL/100 g; JOJOBA OIL 7.5 mL/100 g; TOCOPHEROL 0.75 mL/100 g; HYDROGENATED JOJOBA OIL, RANDOMIZED 0.833 mL/100 g; ORYZANOL 3 mL/100 g; WHITE WAX 6 mL/100 g; CHAMOMILE 0.0005 mL/100 g; LEVOMENOL 0.2 mL/100 g; CALENDULA OFFICINALIS FLOWER 0.0005 mL/100 g; CANDELILLA WAX 9.5 mL/100 g; SHEA BUTTER 1 mL/100 g; RICE BRAN OIL 24.09 mL/100 g; OCTYLDODECYL OLEATE 8.75 mL/100 g; FILIPENDULA ULMARIA FLOWER 0.0005 mL/100 g; COCOA BUTTER 3 mL/100 g; CALOPHYLLUM TACAMAHACA SEED OIL 0.01 mL/100 g; SUNFLOWER OIL 0.098 mL/100 g; AVOCADO OIL 15 mL/100 g; NASTURTIUM OFFICINALE FLOWERING TOP 0.0005 mL/100 g

8065 Babo Baby Face SPF 50 Mineral Sunscreen Stick

Principal Display Panel

Baby Face Mineral Sunscreen

Sheer & Gentle

Broad Spectrum SPF 50

70% Organic Ingredients

Water Resistant (80 Minutes)

Zinc Oxide Mineral Sunscreen

Fragrance Free

Net Wt 0.6 oz / 17 g

DRUG FACTS PANEL

Active Ingredient

Active Ingredient: Zinc Oxide Purpose: Sunscreen

Purpose

Sunscreen

Use

Helps prevent sunburn | If used as directed with other sun protection measures (see Directions), decreases the risk of skin cancer and early skin aging caused by the sun.

Warnings

For external use only. | Do not use on damaged or broken skin. | When using this product Keep out of eyes. Rinse with water to remove. | Stop use and ask doctor if rash occurs. | Keep out of reach of children. If swallowed get medical help or contact a Poison Control center right away. May stain some fabrics and surfaces.

Keep out of reach of children. If swallowed, get medical help or contact a Poison Control center right away.

Directions

- Apply liberally to exposed areas 15 minutes before sun exposure. Children under 6 months: Ask a doctor.
- Reapply:
- after swimming or sweating
- immediately after towel-drying
- at least every 2 hours
- Sun Protection Measures • Spending time in the sun increases your risk of skin cancer and early skin aging. To decrease this risk, regularly use a sunscreen with a broad spectrum SPF of 15 or higher and other protection measures including: Limit time in the sun, especially from 10 a.m. – 2 p.m. and wear long-sleeve shirts, pants, hats, and sunglasses.

Other information

- Protect this product from excessive heat and direct sun.

Inactive ingredients

Oryza Sativa (Rice) Bran Oil*, Persea Gratissima (Avocado) Oil*, Euphorbia Cerifera (Candelilla) Wax, Octyldodecyl Olivate, Simmondsia Chinensis (Jojoba) Seed Oil*, Beeswax*, Theobroma Cacao (Cocoa) Seed Butter*, Oryzanol, Jojoba Esters, Butyrospermum Parkii (Shea) Butter*, Calendula Officinalis Flower Extract*, Chamomilla Recutita (Matricaria) Flower Extract*, Nasturtium Officinale (Watercress) Flower/Leaf Extract*, Spiraea Ulmaria (Meadowsweet) Flower Extract*, Bisabolol*, Calophyllum Inophyllum (Tamanu) Seed Oil*, Helianthus Annuus (Sunflower) Seed Oil*, Tocopherol (Vitamin E).

*Certified Organic Ingredients

Distributed by

Dist: by Babo Botanicals, Inc.
60 East 56th Street New York, NY 10022